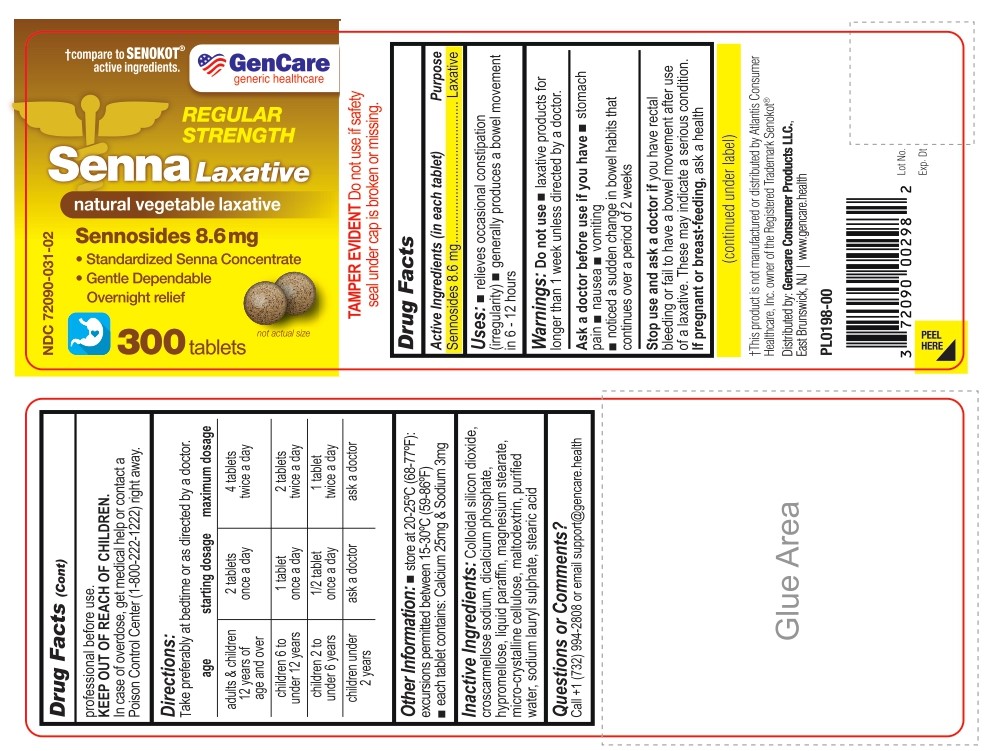 DRUG LABEL: Senna Natural Relief
NDC: 72090-031 | Form: TABLET
Manufacturer: Pioneer Life Sciences, LLC
Category: otc | Type: HUMAN OTC DRUG LABEL
Date: 20251229

ACTIVE INGREDIENTS: SENNOSIDES 8.6 mg/1 1
INACTIVE INGREDIENTS: SODIUM LAURYL SULFATE; MICROCRYSTALLINE CELLULOSE; SILICON DIOXIDE; STEARIC ACID D7; PARAFFIN; DIBASIC CALCIUM PHOSPHATE DIHYDRATE; HYPROMELLOSES; MAGNESIUM STEARATE; MALTODEXTRIN; CROSCARMELLOSE SODIUM

Active Ingredient

Sennosides 8.6 mg

Purpose

Laxative

Uses:

- relieves occasional constipation (irregularity).
- generally prodcues a bowel movement in 6-12 hours

Warnings:

Do not use

- Laxative products for longer than 1 week, unless directed by a doctor.

Ask a doctor before use if you have

- Stomach pain
- nausea
- vomiting,
- Noticed a sudden change in bowel habits that continues over a period of 2 weeks.

Stop use and ask a doctor if you have:

Rectal bleeding or fail to have a bowel movement after use of a laxative.

These may indicate a serious condition.

PREGNANCY OR BREAST FEEDING

If pregnant or breast-feeding, ask a health professional before use.

Keep out of reach of children. In case of overdose, get medical help or contact a Poison Control Center (1-800-222-1222) right away.

DIRECTIONS

- Take preferably at bedtime or as directed by a doctor.

age | starting dosage | maximum dosage
adults & children 12 years of age and over | 2 tablets once a day | 4 tablets twice a day
children 6 to under 12 years | 1 tablet once a day | 2 tablets twice a day
children 2 to under 6 years | 1 /2 tablet once a day | 1 tablet twice a day
children under 2 years | ask a doctor | ask a doctor

OTHER INFORMATION

- store at 20-25°C (68-77°F) excursions permitted between15°-30°C (59°-86°F)
- each tablet contains: Calcium 25 mg & sodium 3 mg

INACTIVE INGREDIENTS

Colloidal silicon dioxide,croscarmellose sodium, Dicalcium phosphate, Hypromellose, liquid paraffin, magnesium stearate, microcrystalline cellulose, Maltodextrin, Purified water, Sodium lauryl sulphate, Stearic Acid.

QUESTIONS OR COMMENTS?

Call + 1-732-994-2808 or email support@gencare.health